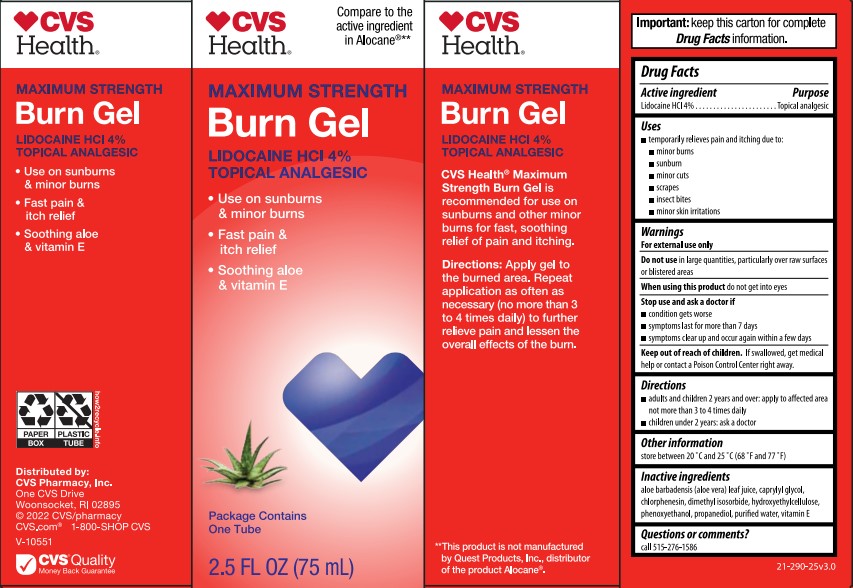 DRUG LABEL: CVS Maximum Strength Burn
NDC: 69842-309 | Form: GEL
Manufacturer: CVS Pharmacy
Category: otc | Type: HUMAN OTC DRUG LABEL
Date: 20251203

ACTIVE INGREDIENTS: LIDOCAINE HYDROCHLORIDE 4 g/100 g
INACTIVE INGREDIENTS: HYDROXYETHYL CELLULOSE (100 MPA.S AT 2%); PHENOXYETHANOL; CAPRYLYL GLYCOL; ALOE VERA LEAF; PROPANEDIOL; DIMETHYL ISOSORBIDE; .ALPHA.-TOCOPHEROL ACETATE; WATER; CHLORPHENESIN

CVS Burn Gel

ACTIVE INGREDIENT

Lidocaine HCl 4%

INDICATIONS AND USAGE

Temporarily relieves pain and itching due to: minor burns, sunburn, minor cuts, scrapes, insect bites, minor skin irritations

WARNINGS

For external use only

DO NOT USE

In large quantities, particularly over raw surfaces or blistered areas

WHEN USING

Do not get into eyes

STOP USE

condition gets worse

symptoms last for more than 7 days

symptoms clear up and occur again within a few days

KEEP OUT OF REACH OF CHILDREN

If swallowed, get medical help or contact a Poison Control Center right away.

Directions

- adults and children 2 years and over: apply to affected area not more than 3 to 4 times daily
- children under 2 years: ask a doctor

PURPOSE

topical analgesic

Other Information

Store between 20 °C and 25 °C (68 °F and 77 °F)

INACTIVE INGREDIENT

Aloe barbadensis (aloe vera) leaf juice, caprylyl glycol, chlorphensin, dimethyl isosorbide, hydroxyethyl cellulose, phenoxyethanol, propanediol, purified water, vitamin E

RECENT MAJOR CHANGES

Uses: Removed title and removed

Directions: Added bullets to separate the requirement

QUESTIONS

call 515-276-1586

PACKAGE LABEL

CVS Health

Maximum Strength Burn Gel

Lidocaine HCl 4%

Topical Analgesic

- Use on sunburns & minor burns
- Past pain & itch relief
- Soothing aloe & vitamin E